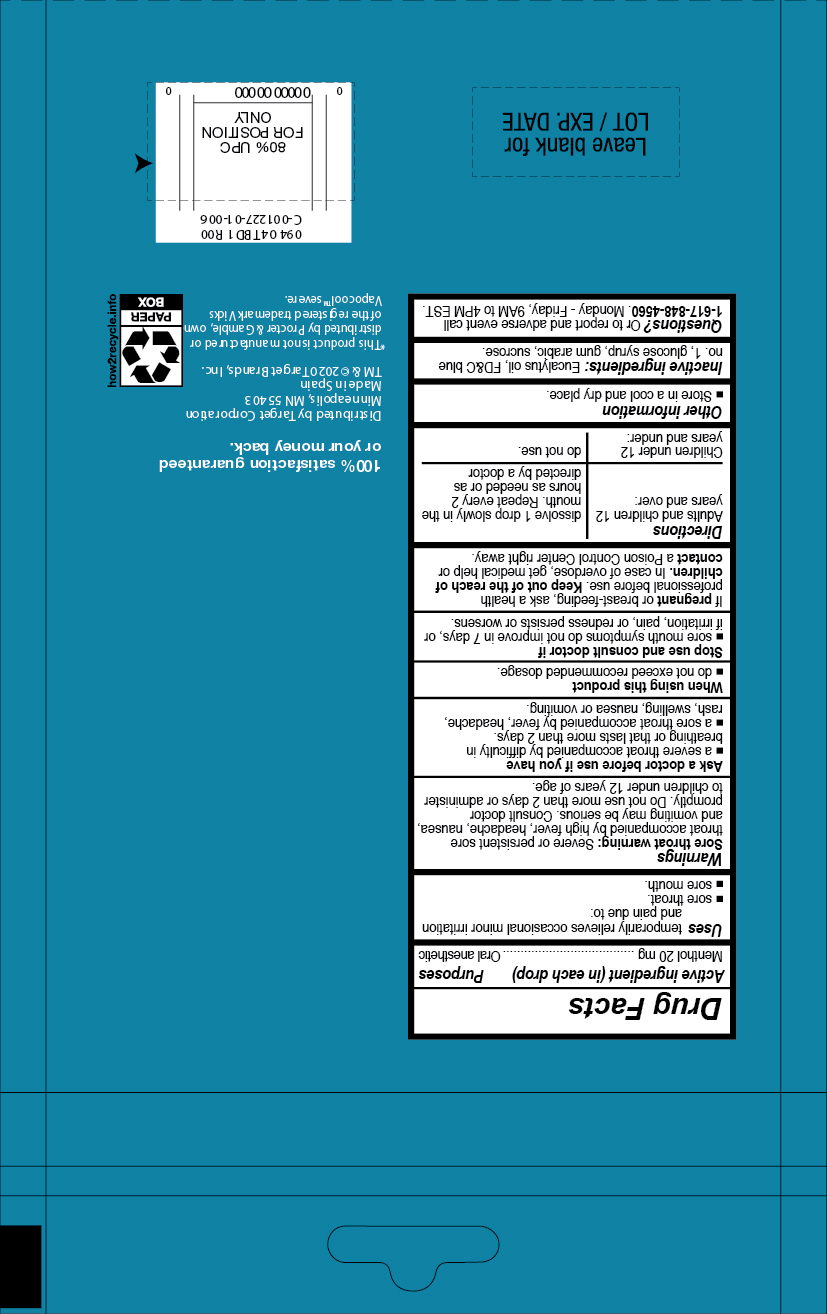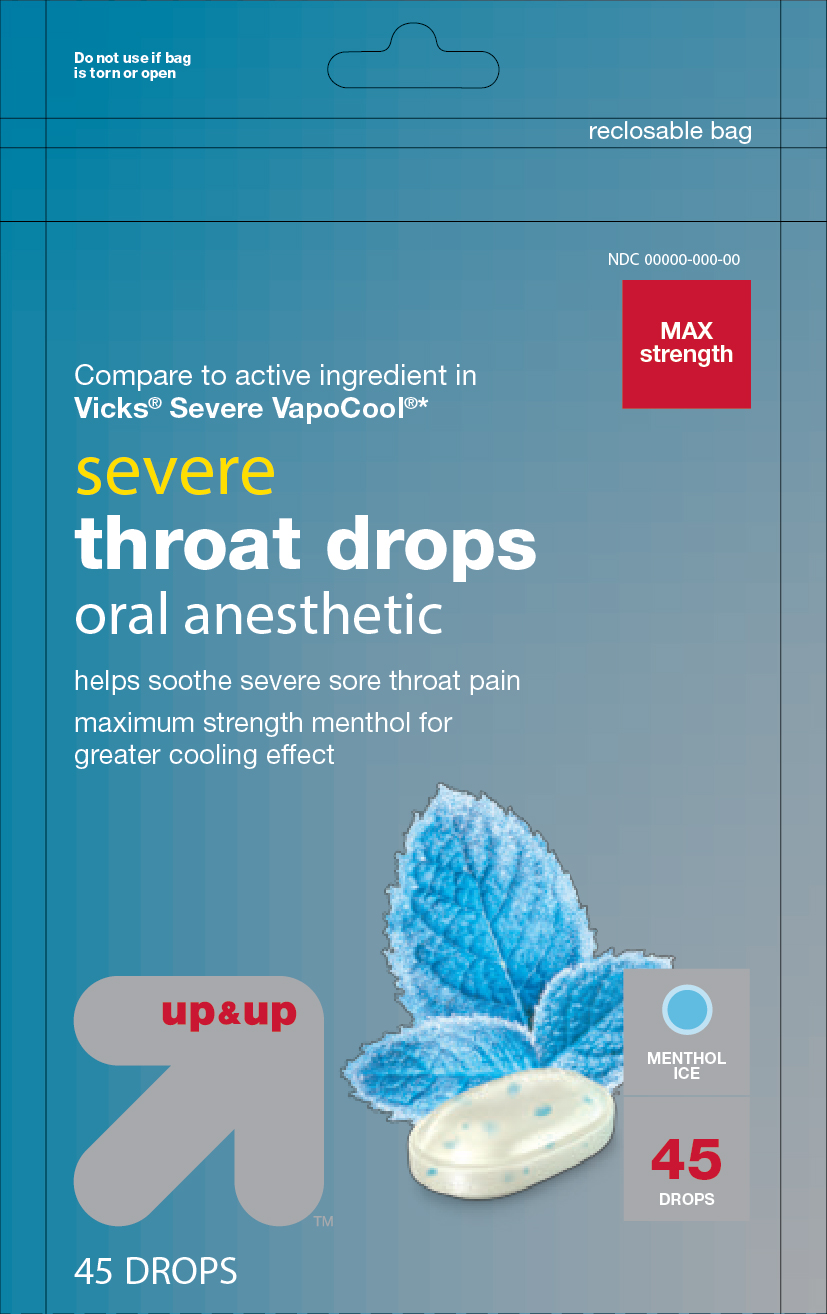 DRUG LABEL: Severe Throat Sore Drops
NDC: 11673-143 | Form: PASTILLE
Manufacturer: Target Corporation Inc.
Category: otc | Type: HUMAN OTC DRUG LABEL
Date: 20241007

ACTIVE INGREDIENTS: MENTHOL 0.69 mg/1 1
INACTIVE INGREDIENTS: EUCALYPTUS OIL; FD&C BLUE NO. 1; WATER; ACACIA; SUCROSE; CORN SYRUP

Severe Throat Drops Oral Anesthetic

Active Ingredient in each drop Purposes

Menthol 20mg Cough Suppressant

Oral anesthetic

PURPOSE

Temporarily relieves ocassional minor irritation and pain due to:

- sore throat
- sore mouth

INDICATIONS AND USAGE

Temporarily relieves ocassional minor irritation and pain due to:

- sore throat
- sore mouth

Warnings

Sore throat warning: severe or persistence sore throat accompanied or followed by high fever, headache, nausea and vomiting may be serious. Consult a doctor promptly. Do not use more than 2 days or administer to children under 12 years of age.

Ask a doctor before use if you have

- a severe throat accompanied by difficulty in breathing or that last more than 2 days
- a sore throat accompanied by fever, headache, rash, swelling, nausea or vomiting

Stop use and consult a doctor if

- sore mouth symptons do not improve in 7 days or if irritation, pains or redness persists or worsens.

PREGNANCY OR BREAST FEEDING

If pregnant or breast-feeding, ask a health professional before use.

KEEP OUT OF REACH OF CHILDREN

Keep this and all drugs out of the reach of children.

OVERDOSAGE

In case of accidental overdose, get medical help or contact a Poison Control Center right away.

Directions

- Adults and children 12 years and over: dissolve 1 drop slowly in mouth. Repeated every 2 hours as needed or as directed by a doctor.
- Children under 12 years and under do not use

OTHER SAFETY INFORMATION

- Store in a cool and dry place

INACTIVE INGREDIENT

eucalyptus oil, FD&C Blue No.1, glucose syrup, gum arabic, sucrose

QUESTIONS

Questions? or to report and adverse event call: 1-617-848-4560

Monday to Friday 9AM to 4 PM east